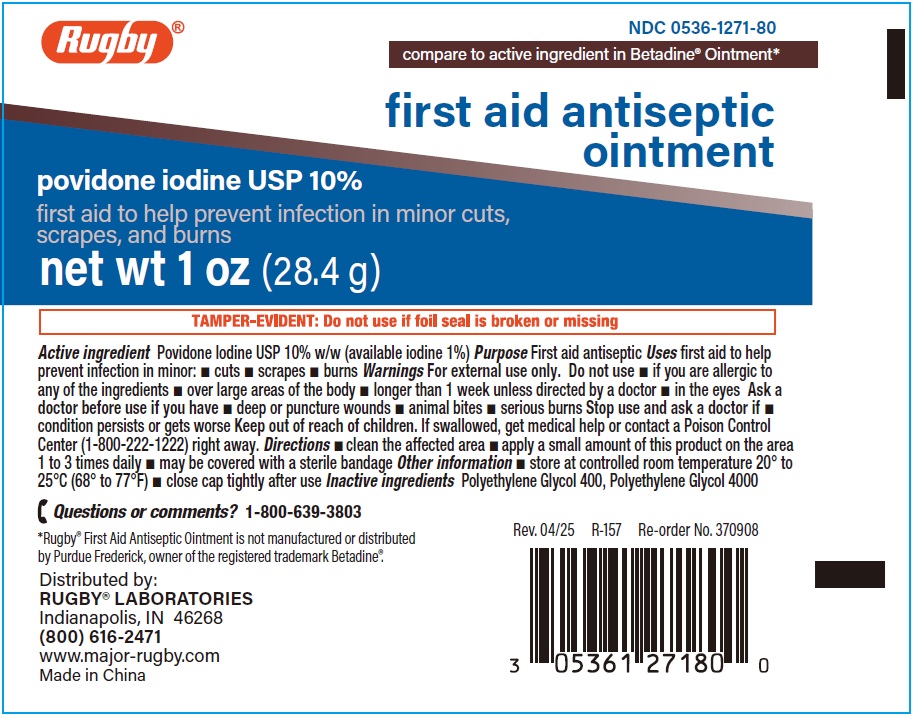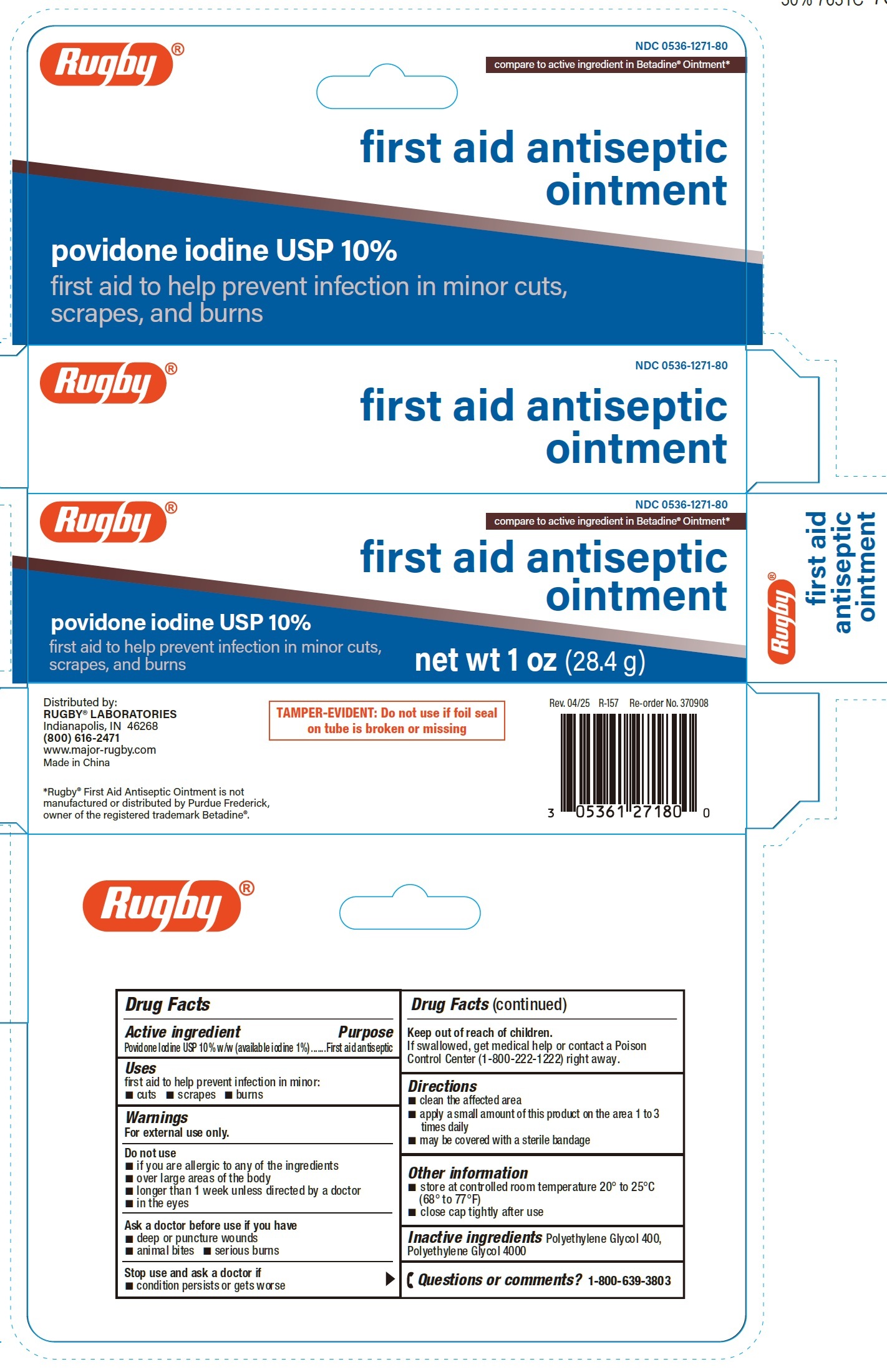 DRUG LABEL: First Aid Antiseptic
NDC: 0536-1271 | Form: OINTMENT
Manufacturer: Rugby Laboratories
Category: otc | Type: HUMAN OTC DRUG LABEL
Date: 20250627

ACTIVE INGREDIENTS: POVIDONE-IODINE 100 mg/1 g
INACTIVE INGREDIENTS: POLYETHYLENE GLYCOL 400; POLYETHYLENE GLYCOL 4000

First Aid Antiseptic Ointment

Active ingredient

Povidone Iodine USP 10% w/w (available iodine 1%)

Purpose

First aid antiseptic

Uses

first aid to help prevent infection in minor:

- cuts
- scrapes
- burns

Warnings

For external use only.

Do not use

- if you are allergic to any of the ingredients
- over large areas of the body
- longer than 1 week unless directed by a doctor
- in the eyes

Ask a doctor before use if you have

- deep or puncture wounds
- animal bites
- serious burns

Stop use and ask a doctor if

condition persists or gets worse

Keep out of reach of children.

If swallowed, get medical help or contact a Poison Control Center (1-800-222-1222) right away.

Directions

- clean the affected area
- apply a small amount of this product on the area 1 to 3 times daily
- may be covered with a sterile bandage

Other information

- store at controlled room temperature 20° to 25°C (68° to 77°F)
- close cap tightly after use

Inactive ingredients

Polyethylene Glycol 400, Polyethylene Glycol 4000

Questions or comments?

1-800-639-3803